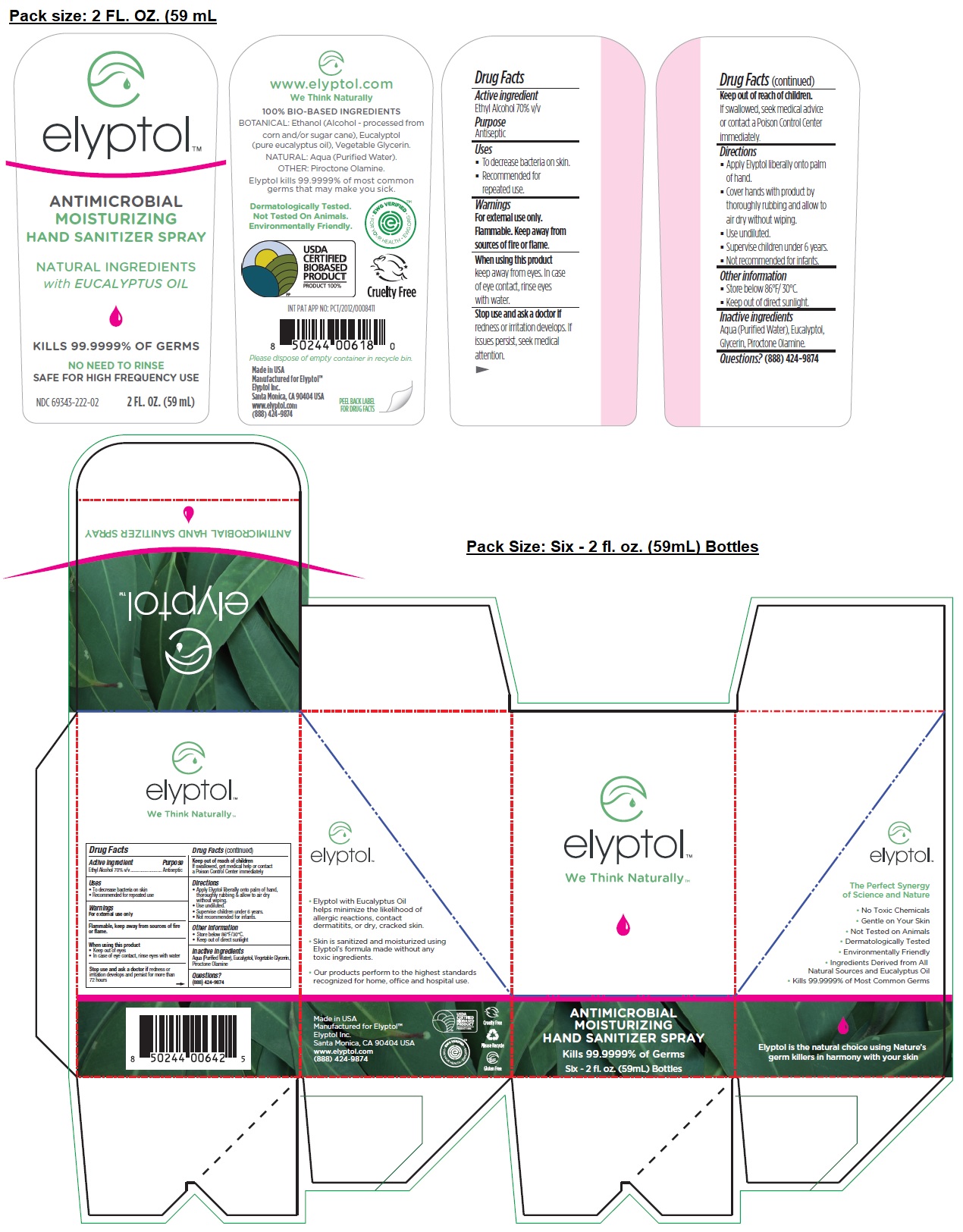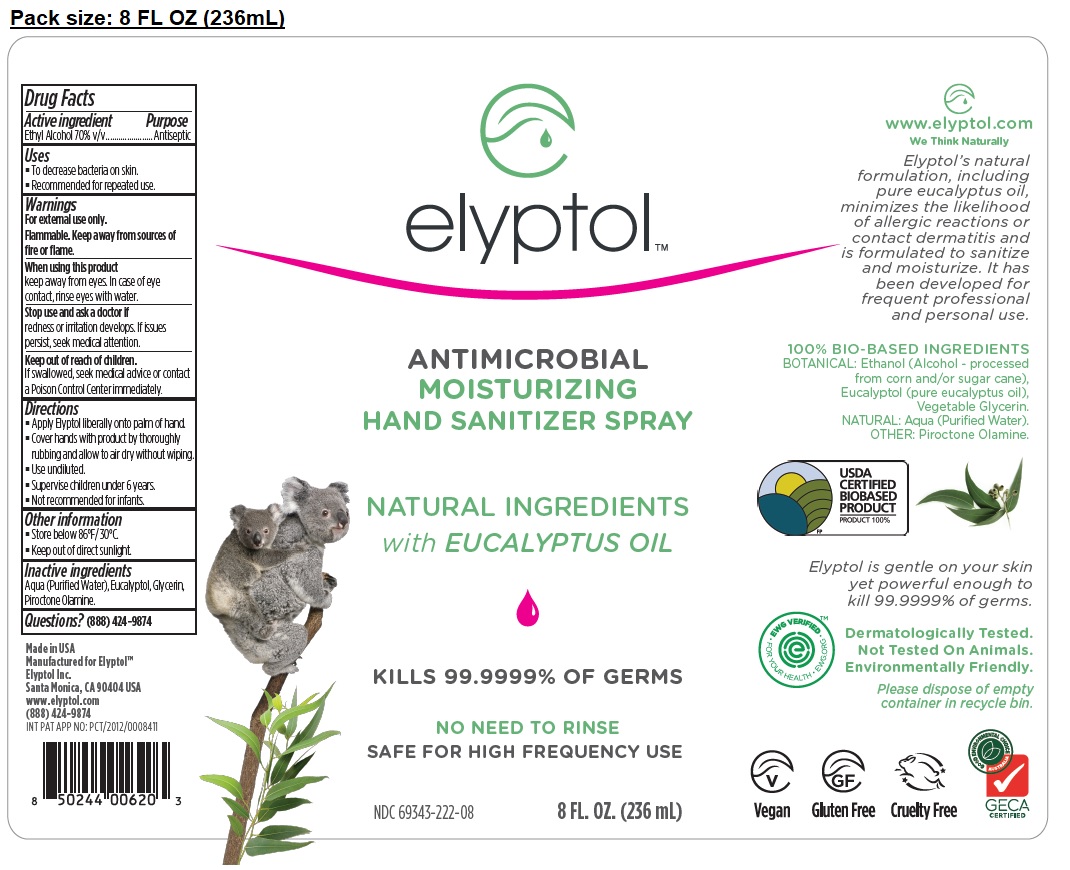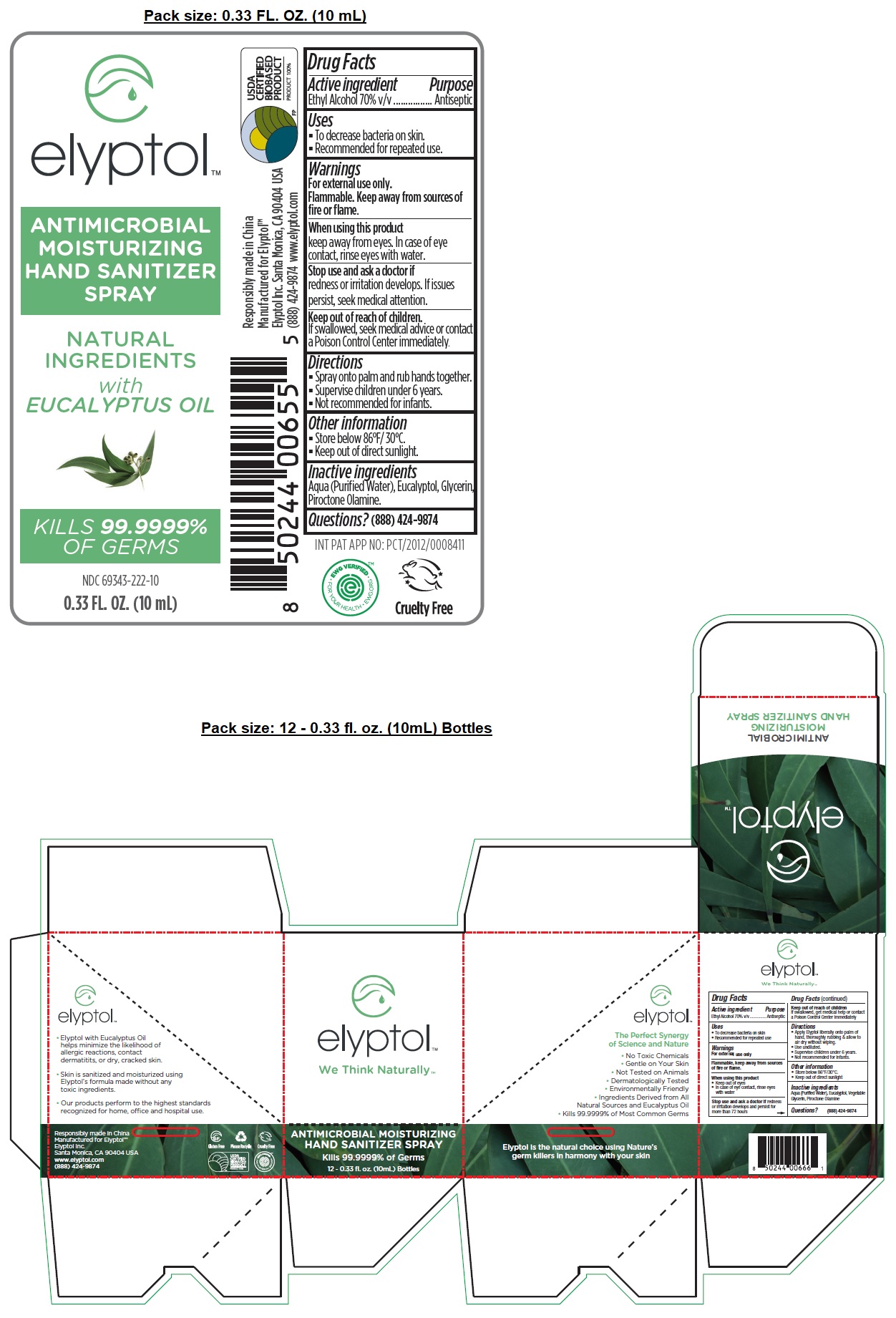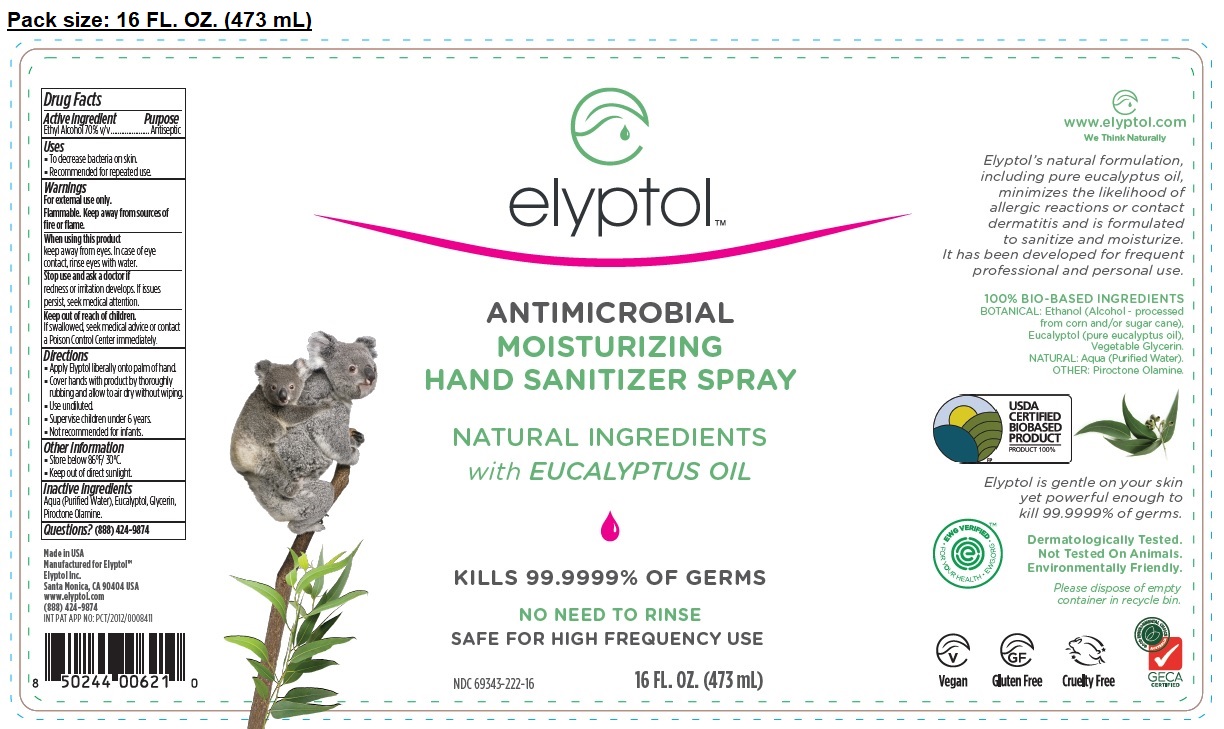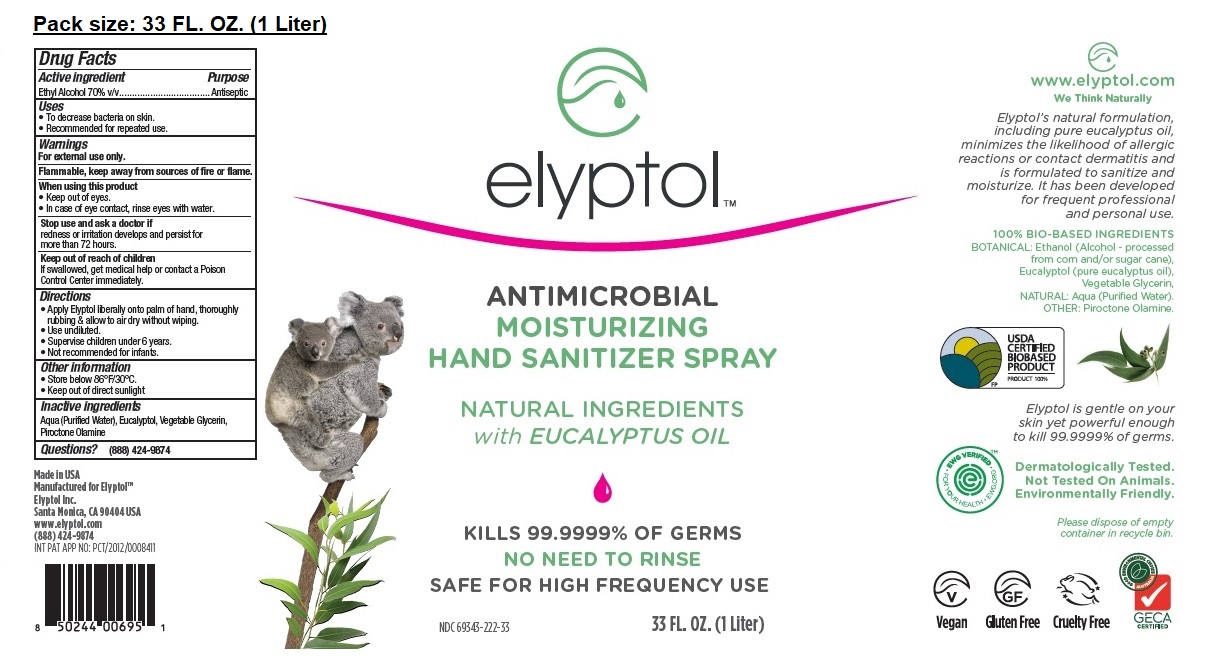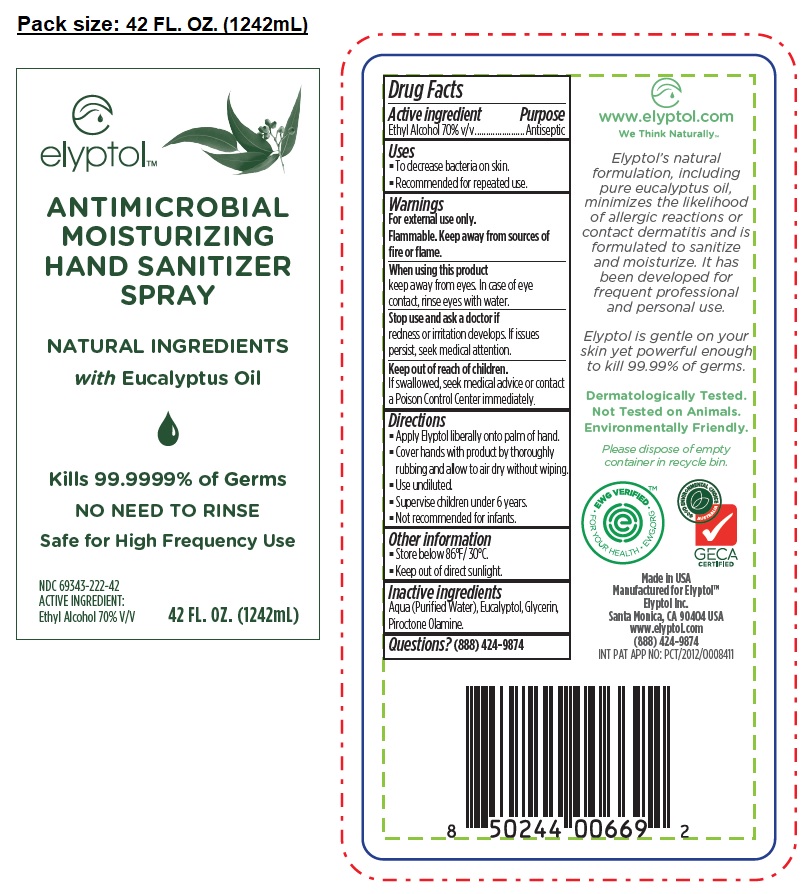 DRUG LABEL: elyptol ANTIMICROBIAL MOISTURIZING HAND SANITIZER
NDC: 69343-222 | Form: SPRAY
Manufacturer: Elyptol Inc.
Category: otc | Type: HUMAN OTC DRUG LABEL
Date: 20221219

ACTIVE INGREDIENTS: ALCOHOL 70 mL/100 mL
INACTIVE INGREDIENTS: WATER; EUCALYPTOL; GLYCERIN; PIROCTONE OLAMINE

elyptol™ ANTIMICROBIAL MOISTURIZING HAND SANITIZER SPRAY

Active ingredient

Ethyl Alcohol 70% v/v

Purpose

Antiseptic

Uses

• To decrease bacteria on skin.

• Recommended for repeated use.

Warnings

For external use only

Flammable, Keep away from sources of fire or flame.

When using this product

• keep out of eyes

• In case of eye contact, rinse eyes with water.

Stop use and ask a doctor if redness or irritation develops and persist for more than 72 hours

Keep out of reach of children

If swallowed, get medical help or contact a Poison Control Center immediately

Directions

• Apply Elyptol liberally onto palm of hand, thoroughly rubbing & allow to air dry without wiping.

• Use undiluted.

• Supervise children under 6 years.

• Not recommended for infants.

Other information

• Store below 86°F/30°C.

• Keep out of direct sunlight

Inactive ingredients

Aqua (Purified Water), Eucalyptol, Vegetable Glycerin, Piroctone Olamine

Questions? (888) 424-9874

NATURAL INGREDIENTS with EUCALYPTUS OIL

NO NEED TO RINSE
SAFE FOR HIGH FREQUENCY USE

We Think Naturally™

Kills 99.9999% of Germs

• Elyptol with Eucalyptus Oil helps minimize the likelihood of allergic reactions, contact dermatitis, or dry, cracked skin.

• Skin is sanitized and moisturized using Elyptol’s formula made without any toxic ingredients.

• Our products perform to the highest standards recognized for home, office and hospital use.

The Perfect Synergy of Science and Nature

• No Toxic Chemicals
• Gentle on Your Skin
• Not Tested on Animals
• Dermatologically Tested
• Environmentally Friendly
• Ingredients Derived from All Natural Sources and Eucalyptus Oil
• Kills 99.9999% of Most Common Germs

Manufactured for Elyptol™

Elyptol Inc.

Santa Monica, CA 90404 USA

www.elyptol.com

(888) 424-9874

Elyptol is the natural choice using Nature’s germ killers in harmony with your skin

Vegan

Gluten Free

Please Recycle

Cruelty Free

Dermatologically Tested.
Not Tested On Animals.
Environmentally Friendly.
Please dispose of empty container in recycle bin.

EWG VERIFIED • EWG.ORG • FOR YOUR HEALTH